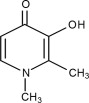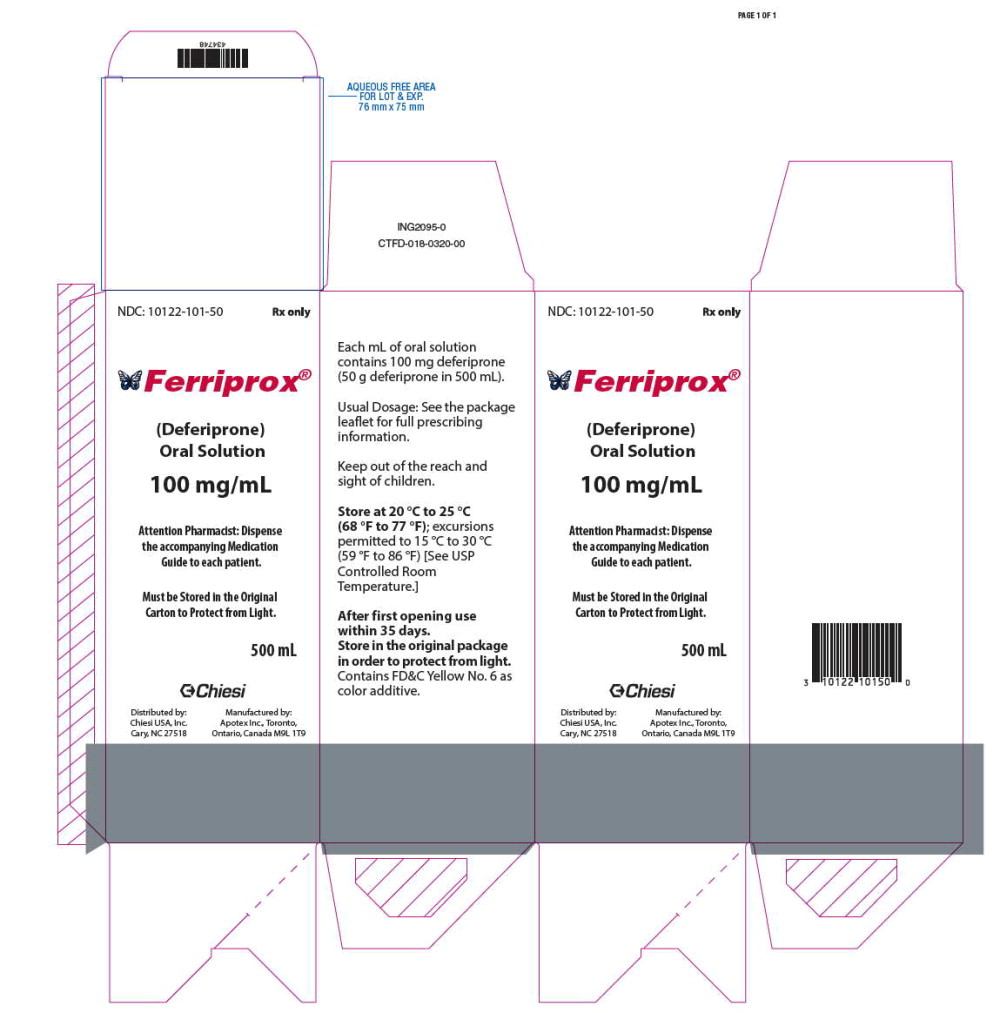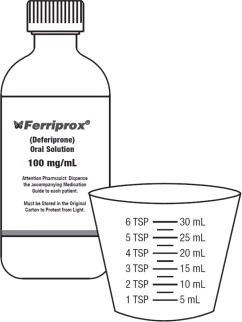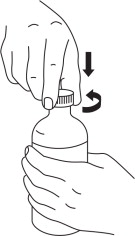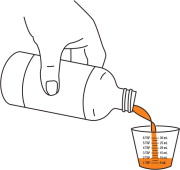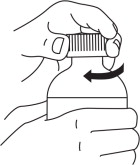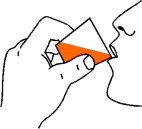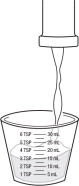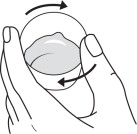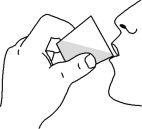 DRUG LABEL: FERRIPROX
NDC: 10122-101 | Form: SOLUTION
Manufacturer: Chiesi USA, Inc.
Category: prescription | Type: HUMAN PRESCRIPTION DRUG LABEL
Date: 20250522

ACTIVE INGREDIENTS: DEFERIPRONE 100 mg/1 mL
INACTIVE INGREDIENTS: Water; Hydroxyethyl Cellulose (2000 Cps At 1%); Glycerin; Hydrochloric Acid; Peppermint Oil; Fd&C Yellow No. 6; Sucralose

HIGHLIGHTS OF PRESCRIBING INFORMATION

These highlights do not include all the information needed to use FERRIPROX Oral Solution safely and effectively. See full prescribing information for FERRIPROX Oral Solution.
FERRIPROX® (deferiprone) oral solution, for oral use
Initial U.S. Approval: 2011

RECENT MAJOR CHANGES

Warnings and Precautions, Agranulocytosis and Neutropenia (5.1) | 3/2025

WARNING: AGRANULOCYTOSIS AND NEUTROPENIA

See full prescribing information for complete boxed warning.

- FERRIPROX can cause agranulocytosis that can lead to serious infections and death. Neutropenia may precede the development of agranulocytosis. (5.1)
- Measure the absolute neutrophil count (ANC) before starting FERRIPROX and monitor regularly while on therapy. (5.1)
- Interrupt FERRIPROX therapy if neutropenia develops. (5.1)
- Interrupt FERRIPROX if infection develops and monitor the ANC more frequently. (5.1)
- Advise patients taking FERRIPROX to report immediately any symptoms indicative of infection. (5.1)

1 INDICATIONS AND USAGE

FERRIPROX Oral Solution is an iron chelator indicated for the treatment of transfusional iron overload in adult and pediatric patients 3 years of age and older with thalassemia syndromes, sickle cell disease or other anemias. (1)

Limitations of Use

Safety and effectiveness have not been established for the treatment of transfusional iron overload in patients with myelodysplastic syndrome or in patients with Diamond Blackfan anemia.

2 DOSAGE AND ADMINISTRATION

25 mg/kg to 33 mg/kg actual body weight, orally, three times per day, for a total daily dose of 75 mg/kg to 99 mg/kg body weight. (2.1)

3 DOSAGE FORMS AND STRENGTHS

Oral Solution: 100 mg/mL (50 g/500 mL) (3)

4 CONTRAINDICATIONS

Hypersensitivity to deferiprone or to any of the excipients in the formulation. (4)

5 WARNINGS AND PRECAUTIONS

- Liver Enzyme Elevations: Monitor monthly and discontinue for persistent elevations. (5.2)
- Zinc Deficiency: Monitor during therapy and supplement for deficiency. (5.3)
- Embryo-Fetal Toxicity: Can cause fetal harm. (5.4)

6 ADVERSE REACTIONS

- The most common adverse reactions in patients with thalassemia (incidence ≥ 6%) are nausea, vomiting, abdominal pain, arthralgia, ALT increased and neutropenia. (6)
- The most common adverse reactions in patients with sickle cell disease or other anemias (incidence ≥6%) are pyrexia, abdominal pain, bone pain, headache, vomiting, pain in extremity, sickle cell anemia with crisis, back pain, ALT increased, AST increased, arthralgia, oropharyngeal pain, nasopharyngitis, neutrophil count decreased, cough and nausea. (6)

To report SUSPECTED ADVERSE REACTIONS, contact Chiesi USA, Inc. at 1-888-661-9260 or FDA at 1-800-FDA-1088 or www.fda.gov/medwatch

7 DRUG INTERACTIONS

- Drugs Associated with Neutropenia or Agranulocytosis: Avoid co-administration. If co-administration is unavoidable, closely monitor the absolute neutrophil count. (7.1)
- UGT1A6 Inhibitors: Avoid co-administration. (7.2)
- Polyvalent Cations: Allow at least a 4-hour interval between administration of FERRIPROX and drugs or supplements containing polyvalent cations (e.g., iron, aluminum, or zinc). (2.2, 7.2)

8 USE IN SPECIFIC POPULATIONs

Lactation: Advise not to breastfeed. (8.2)

FULL PRESCRIBING INFORMATION

WARNING: AGRANULOCYTOSIS AND NEUTROPENIA

- FERRIPROX can cause agranulocytosis that can lead to serious infections and death. Neutropenia may precede the development of agranulocytosis. [see Warnings and Precautions (5.1)]
- Measure the absolute neutrophil count (ANC) before starting FERRIPROX therapy and monitor regularly while on therapy. [see Warnings and Precautions (5.1)]
- Interrupt FERRIPROX therapy if neutropenia develops. [see Warnings and Precautions (5.1)]
- Interrupt FERRIPROX if infection develops, and monitor the ANC more frequently. [see Warnings and Precautions (5.1)]
- Advise patients taking FERRIPROX to report immediately any symptoms indicative of infection. [see Warnings and Precautions (5.1)]

1 INDICATIONS AND USAGE

FERRIPROX Oral Solution is indicated for the treatment of transfusional iron overload in adult and pediatric patients 3 years of age and older with thalassemia syndromes, sickle cell disease or other anemias.

Limitations of Use

- Safety and effectiveness have not been established for the treatment of transfusional iron overload in patients with myelodysplastic syndrome or in patients with Diamond Blackfan anemia.

2 DOSAGE AND ADMINISTRATION

2.1 Important Dosage and Administration Information

Monitoring for Safety

Due to the risk of agranulocytosis, monitor ANC before and during FERRIPROX therapy.

Test ANC prior to start of FERRIPROX therapy and monitor on the following schedule during treatment:

- First six months of therapy: Monitor ANC weekly;
- Next six months of therapy: Monitor ANC once every two weeks;
- After one year of therapy: Monitor ANC every two to four weeks (or at the patient's blood transfusion interval in patients that have not experienced an interruption due to any decrease in ANC [see Warnings and Precautions (5.1)].

Due to the risk of hepatic transaminase elevations, monitor ALT before and monthly during FERRIPROX therapy [see Warnings and Precautions (5.2)].

Due to the risk of zinc deficiency, monitor zinc levels before and regularly during FERRIPROX therapy [see Warnings and Precautions (5.3)].

2.2 Recommended Dosage for FERRIPROX Oral Solution for Adult and Pediatric Patients with Transfusional Iron Overload due to Thalassemia Syndromes, Sickle Cell Disease or Other Anemias

Starting Dosage

The recommended starting oral dosage of FERRIPROX Oral Solution is 25 mg/kg (actual body weight), three times per day for a total of 75 mg/kg/day. Round dose to the nearest 2.5 mL.

Table 1: Volume of FERRIPROX Oral Solution in mL Needed to Achieve the Total Starting Daily Dosage of 75 mg/kg (rounded to the nearest 2.5 mL)
Body Weight (kg) | Morning | Midday | Evening
20 | 5 | 5 | 5
30 | 7.5 | 7.5 | 7.5
40 | 10 | 10 | 10
50 | 12.5 | 12.5 | 12.5
60 | 15 | 15 | 15
70 | 17.5 | 17.5 | 17.5
80 | 20 | 20 | 20
90 | 22.5 | 22.5 | 22.5

To minimize gastrointestinal upset when first starting therapy, dosing can start at 45 mg/kg/day and increase weekly by 15 mg/kg/day increments until the full prescribed dose is achieved.

Dosage Adjustments

Tailor dosage adjustments to the individual patient's response and therapeutic goals (maintenance or reduction of body iron burden). The maximum oral dosage is 33 mg/kg (actual body weight), three times per day for a total of 99 mg/kg/day.

Table 2: Volume of FERRIPROX Oral Solution in mL Needed to Achieve the Maximum Total Daily Dosage of 99 mg/kg (rouded to the nearest 2.5 mL)
Body Weight (kg) | Morning | Midday | Evening
20 | 7.5 | 5 | 7.5
30 | 10 | 10 | 10
40 | 15 | 10 | 15
50 | 17.5 | 15 | 17.5
60 | 20 | 20 | 20
70 | 25 | 22.5 | 22.5
80 | 27.5 | 25 | 27.5
90 | 30 | 30 | 30

2.3 Monitoring Ferritin Levels to Assess Efficacy

Monitor serum ferritin concentration every two to three months to assess the effect of FERRIPROX on body iron stores. If the serum ferritin is consistently below 500 mcg/L, consider temporarily interrupting FERRIPROX therapy until serum ferritin rises above 500 mcg/L.

2.4 Dosage Modification for Drug Interactions

Allow at least a 4-hour interval between administration of FERRIPROX and other drugs or supplements containing polyvalent cations such as iron, aluminum, or zinc [see Drug Interactions (7.2), Clinical Pharmacology (12.3)].

3 DOSAGE FORMS AND STRENGTHS

Oral Solution: 100 mg/mL (50 g/500 mL), clear, reddish orange colored solution.

4 CONTRAINDICATIONS

FERRIPROX is contraindicated in patients with known hypersensitivity to deferiprone or to any of the excipients in the formulation. The following reactions have been reported in association with the administration of deferiprone: Henoch-Schönlein purpura; urticaria; and periorbital edema with skin rash [see Adverse Reactions (6.2)].

5 WARNINGS AND PRECAUTIONS

5.1 Agranulocytosis and Neutropenia

Fatal agranulocytosis can occur with FERRIPROX use. FERRIPROX can also cause neutropenia, which may foreshadow agranulocytosis. Measure the absolute neutrophil count (ANC) before starting FERRIPROX therapy and monitor it regularly while on therapy.

Reduction in the frequency of ANC monitoring should be considered on an individual patient basis, according to the health care provider's assessment of the patient's understanding of the risk minimization measures required during therapy.

Interrupt FERRIPROX therapy if neutropenia develops (ANC < 1.5 x 10^9/L).

Interrupt FERRIPROX if infection develops and monitor the ANC frequently.

Advise patients taking FERRIPROX to immediately interrupt therapy and report to their physician if they experience any symptoms indicative of infection.

The incidence of agranulocytosis was 1% of patients in pooled clinical trials of 642 patients with thalassemia syndromes and 0.5% of patients in pooled clinical trials of 196 patients with sickle cell disease or other anemias. The mechanism of FERRIPROX-associated agranulocytosis is unknown. Agranulocytosis and neutropenia usually resolve upon discontinuation of FERRIPROX, but there have been reports of agranulocytosis leading to death.

Implement a plan to monitor for and to manage agranulocytosis and neutropenia prior to initiating FERRIPROX treatment.

For agranulocytosis (ANC < 0.2 x 10^9/L) and severe neutropenia (0.2 x 10^9/L ≤ ANC < 0.5 x 10^9/L):

Consider hospitalization and other management as clinically appropriate.

Do not resume FERRIPROX in patients who have developed agranulocytosis unless potential benefits outweigh potential risks. Do not rechallenge patients who have developed neutropenia with FERRIPROX unless potential benefits outweigh potential risks.

For neutropenia (ANC < 1.5 x 10^9/L and ≥ 0.5 x 10^9/L):

Instruct the patient to immediately discontinue FERRIPROX and all other medications with a potential to cause neutropenia.

Obtain a complete blood cell (CBC) count, including a white blood cell (WBC) count corrected for the presence of nucleated red blood cells, an absolute neutrophil count (ANC), and a platelet count daily until recovery (ANC ≥ 1.5 x 10^9/L).

5.2 Liver Enzyme Elevations

In pooled clinical trials, 7.5% of 642 patients with thalassemia syndromes treated with FERRIPROX developed increased ALT values. Four (0.62%) FERRIPROX-treated subjects discontinued the drug due to increased serum ALT levels and 1 (0.16%) due to an increase in both ALT and AST. In pooled clinical trials, 7.7% of 196 patients with sickle cell disease or other anemias treated with FERRIPROX developed increased ALT values.

Monitor serum ALT values monthly during therapy with FERRIPROX and consider interruption of therapy if there is a persistent increase in the serum transaminase levels [see Dosage and Administration (2.1)].

5.3 Zinc Deficiency

Decreased plasma zinc concentrations have been observed on FERRIPROX therapy. Monitor plasma zinc annually, and supplement in the event of a deficiency [see Dosage and Administration (2.1)].

5.4 Embryo-Fetal Toxicity

Based on findings from animal reproduction studies and evidence of genotoxicity, FERRIPROX can cause fetal harm when administered to a pregnant woman. The available data on the use of FERRIPROX in pregnant women are insufficient to inform risk. In animal studies, administration of deferiprone during the period of organogenesis resulted in embryo-fetal death and malformations at doses lower than equivalent human clinical doses. Advise pregnant women and females of reproductive potential of the potential risk to the fetus [see Use in Specific Populations (8.1)].

Advise females of reproductive potential to use an effective method of contraception during treatment with FERRIPROX and for at least six months after the last dose. Advise males with female partners of reproductive potential to use effective contraception during treatment with FERRIPROX and for at least three months after the last dose [see Use in Specific Populations (8.1, 8.3)].

6 ADVERSE REACTIONS

The following clinically significant adverse reactions are described below and elsewhere in the labeling:

- Agranulocytosis and Neutropenia [see Warnings and Precautions (5.1)]
- Liver Enzyme Elevations [see Warnings and Precautions (5.2)]
- Zinc Deficiency [see Warnings and Precautions (5.3)]

6.1 Clinical Trial Experience

Because clinical trials are conducted under widely varying conditions, adverse reaction rates observed in the clinical trials of a drug cannot be directly compared to rates in the clinical trials of another drug and may not reflect the rates observed in practice.

The following adverse reaction information represents the pooled data collected from single arm or active-controlled clinical trials with FERRIPROX Tablets (deferiprone) (three times a day) or FERRIPROX Oral Solution (deferiprone).

Thalassemia Syndromes

The safety of FERRIPROX was evaluated in the pooled clinical trial database [see Clinical Studies (14.1)]. Patients received FERRIPROX Tablets (three times a day) or FERRIPROX Oral Solution. FERRIPROX was administered orally three times a day (total daily dose either 50, 75, or 99 mg/kg), N=642. Among 642 patients receiving FERRIPROX, 492 (76.6%) were exposed for 6 months or longer and 365 (56.9%) were exposed for greater than one year.

The median age of patients who received FERRIPROX was 19 years (range 1, 77 years); 50.2% female; 71.2% White, 17.8% Asian, 9.2% Unknown, 1.2% Multi-racial and 0.6% Black.

The most serious adverse reaction reported in clinical trials with FERRIPROX was agranulocytosis [see Warnings and Precautions (5.1)].

The most common adverse reactions (≥6%) reported during clinical trials were nausea, vomiting, abdominal pain, arthralgia, alanine aminotransferase increased and neutropenia.

The table below lists the adverse drug reactions that occurred in at least 1% of patients treated with FERRIPROX in clinical trials in patients with thalassemia syndromes.

Table 3: Adverse reactions occurring in ≥ 1% of FERRIPROX-treated patients with thalassemia syndromes
Body System Adverse Reaction | (N=642) % Patients
BLOOD AND LYMPHATIC SYSTEM DISORDERS
Neutropenia* | 7
Agranulocytosis† | 1
GASTROINTESTINAL DISORDERS
Nausea | 13
Abdominal pain/discomfort | 10
Vomiting | 10
Diarrhea | 3
Dyspepsia | 2
INVESTIGATIONS
Alanine aminotransferase increased | 7
Weight increased | 2
Aspartate aminotransferase increased | 1
METABOLISM AND NUTRITION DISORDERS
Increased appetite | 4
Decreased appetite | 1
MUSCULOSKELETAL AND CONNECTIVE TISSUE DISORDERS
Arthralgia | 10
Back pain | 2
Pain in extremity | 2
Arthropathy | 1
NERVOUS SYSTEM DISORDERS
Headache | 2
*Neutropenia includes events of severe neutropenia (ANC ≥0.2 x 10^9/L and <0.5 x 10^9/L).
†Agranulocytosis (ANC< 0.2 x 10^9/L)

Gastrointestinal symptoms such as nausea, vomiting, and abdominal pain were the most frequent adverse reactions reported by patients participating in clinical trials and led to the discontinuation of FERRIPROX therapy in 1.6% of patients.

Chromaturia (reddish/brown discoloration of the urine) is a result of the excretion of iron in the urine.

Sickle Cell Disease or Other Anemias

The safety of FERRIPROX compared to deferoxamine was evaluated in LA38-0411 [see Clinical Studies (14.2)]. Patients received FERRIPROX Tablets or FERRIPROX Oral Solution orally three times a day (total daily dose 75-99 mg/kg/day) n=152) or the control arm, deferoxamine, 20-40 mg/kg/day (children) or 40-50 mg/kg/day (adults), by subcutaneous infusion for 5 – 7 days per week, n=76. Among 152 patients receiving FERRIPROX, 120 (78.9%) were exposed for 6 months or longer and 17 (11.2%) were exposed for greater than one year.

The median age of patients who received FERRIPROX was 15 years (range 3, 59 years); 54.6% male; 78.9% White, 15.1% Black and 5.9% Multi-racial.

The most common adverse reactions (≥6%) reported during clinical trials in patients with SCD or other anemias were pyrexia, abdominal pain, bone pain, headache, vomiting, pain in extremity, sickle cell anemia with crisis, back pain, alanine aminotransferase (ALT) increased, aspartate aminotransferase (AST) increased, arthralgia, oropharyngeal pain, nasopharyngitis, neutrophil count decreased, cough and nausea.

The table below lists the adverse reactions (irrespective of a causal assessment; adverse events) of interest that occurred in patients treated with FERRIPROX in clinical trials in subjects with sickle cell disease or other anemias.

Table 4: Adverse reactions occurring in ≥5% of FERRIPROX-treated patients with sickle cell disease or other anemias
Body System Adverse Reaction | FERRIPROX (N=152) % Patients | DEFEROXAMINE (N=76) % Patients
BLOOD AND LYMPHATIC SYSTEM DISORDERS
Sickle cell anemia with crisis | 17 | 13
GASTROINTESTINAL DISORDERS
Abdominal pain* | 26 | 13
Vomiting | 19 | 11
Nausea | 7 | 9
Diarrhea | 5 | 8
GENERAL DISORDERS AND ADMINISTRATION SITE CONDITIONS
Pyrexia | 28 | 33
Pain | 5 | 4
INFECTIONS AND INFESTATIONS
Nasopharyngitis | 9 | 12
Upper respiratory tract infection | 5 | 3
INVESTIGATIONS
Alanine aminotransferase increased | 12 | 0
Aspartate aminotransferase increased | 11 | 0
Neutrophil count decreased | 8 | 4
MUSCULOSKELETAL AND CONNECTIVE TISSUE DISORDERS
Bone pain | 25 | 34
Pain in extremity | 18 | 15
Back pain | 13 | 18
Arthralgia | 10 | 8
NERVOUS SYSTEM DISORDERS
Headache | 20 | 13
RESPIRATORY, THORACIC AND MEDIASTINAL DISORDERS
Oropharyngeal pain | 10 | 15
Cough | 8 | 15
*Grouped term

Clinically relevant adverse reactions in <5% of patients include neutropenia and agranulocytosis.

Pediatric Patients

FERRIPROX has been studied in 86 pediatric patients with sickle cell disease or other anemias. Pediatric patients (<17 years) had an increase in the following adverse reactions as compared to adults: abdominal pain, neutrophil count decreased, bone pain and oropharyngeal pain.

6.2 Postmarketing Experience

The following additional adverse reactions have been reported in patients receiving FERRIPROX. Because these reactions are reported voluntarily from a population of uncertain size, it is not always possible to reliably estimate their frequency or to establish a causal relationship to drug exposure.

Blood and lymphatic system disorders: thrombocytosis, pancytopenia.

Cardiac disorders: atrial fibrillation, cardiac failure.

Congenital, familial and genetic disorders: hypospadias.

Eye disorders: diplopia, papilledema, retinal toxicity.

Gastrointestinal disorders: enterocolitis, rectal hemorrhage, gastric ulcer, pancreatitis, parotid gland enlargement.

General disorders and administration site conditions: chills, edema peripheral, multi-organ failure.

Hepatobiliary disorders: jaundice, hepatomegaly.

Immune system disorders: anaphylactic shock, hypersensitivity.

Infections and infestations: cryptococcal cutaneous infection, enteroviral encephalitis, pharyngitis, pneumonia, sepsis, furuncle, infectious hepatitis, rash pustular, subcutaneous abscess.

Investigations: blood bilirubin increased, blood creatinine phosphokinase increased.

Metabolism and nutrition disorders: metabolic acidosis, dehydration.

Musculoskeletal and connective tissue disorders: myositis, chondropathy, trismus.

Nervous system disorders: cerebellar syndrome, cerebral hemorrhage, convulsion, gait disturbance, intracranial pressure increased, psychomotor skills impaired, pyramidal tract syndrome, somnolence.

Psychiatric disorders: bruxism, depression, obsessive-compulsive disorder.

Renal disorders: glycosuria, hemoglobinuria.

Respiratory, thoracic and mediastinal disorders: acute respiratory distress syndrome, epistaxis, hemoptysis, pulmonary embolism.

Skin, subcutaneous tissue disorders: hyperhidrosis, periorbital edema, photosensitivity reaction, pruritis, urticaria, rash, Henoch-Schönlein purpura.

Vascular disorders: hypotension, hypertension.

7 DRUG INTERACTIONS

7.1 Drugs Associated with Neutropenia or Agranulocytosis

Avoid co-administration of FERRIPROX with other drugs known to be associated with neutropenia or agranulocytosis. If co-administration is unavoidable, closely monitor the absolute neutrophil count [see Warnings and Precautions (5.1)].

7.2 Effect of Other Drugs on FERRIPROX

UDP-Glucuronosyltransferases (UGT)

Avoid use of UGT1A6 inhibitors (e.g., diclofenac, probenecid, or silymarin (milk thistle)) with FERRIPROX [see Dosage and Administration (2.2), Adverse Reactions (6.1), Clinical Pharmacology (12.3)].

Polyvalent Cations

Deferiprone has the potential to bind polyvalent cations (e.g., iron, aluminum, and zinc); allow at least a 4-hour interval between FERRIPROX and other medications (e.g., antacids), or supplements containing these polyvalent cations [see Dosage and Administration (2.2)].

8 USE IN SPECIFIC POPULATIONs

8.1 Pregnancy

Risk Summary

In animal reproduction studies, oral administration of deferiprone to pregnant rats and rabbits during organogenesis at doses 33% and 49%, respectively, of the maximum recommended human dose (MRHD) resulted in structural abnormalities, embryo-fetal mortality and alterations to growth (see Data). The limited available data from deferiprone use in pregnant women are insufficient to inform a drug-associated risk of major birth defects and miscarriage. Based on evidence and developmental toxicity in animal studies, FERRIPROX can cause fetal harm when administered to a pregnant woman. Advise pregnant women and females of reproductive potential of the potential risk to a fetus.

The estimated background risk of major birth defects and miscarriage for the indicated population is unknown. All pregnancies have a background risk of birth defect, loss, or other adverse outcomes. In the U.S. general population, the estimated background risk of major birth defects and of miscarriage is 2-4% and 15-20%, respectively.

Data

Human Data

Post-marketing data available from 39 pregnancies of deferiprone-treated patients and 10 pregnancies of partners of deferiprone-treated patients are as follows:

Of the 39 pregnancies in deferiprone-treated patients, 23 resulted in healthy newborns, 6 ended in spontaneous abortion, 9 had unknown outcomes, and 1 infant was born with anal atresia, nephroptosis, ventricular septal defect, hemivertebra and urethral fistula.

Of the 10 pregnancies in partners of deferiprone-treated patients, 5 resulted in healthy newborns, 1 resulted in a healthy newborn with slight hypospadias, 1 was electively terminated, 1 resulted in the intrauterine death of twins, and 2 had unknown outcomes.

Animal Data

During organogenesis, pregnant rats and rabbits received deferiprone at oral doses of 0, 30, 80 or 200 mg/kg/day, and 0, 10, 50, or 150 mg/kg/day, respectively. The daily dose was administered as two equal divided doses approximately 7 hours apart. Doses of 200 mg/kg/day in rats and 150 mg/kg/day in rabbits, approximately 33% and 49% of the MRHD, respectively, resulted in increased post-implantation loss and reduced fetal weights in the presence of maternal toxicity (reduced maternal body weight and body weight gain in both rats and rabbits; abnormal large placenta at low incidence in rats). The 200 mg/kg/day dose in rats resulted in external, visceral and skeletal fetal malformations such as cranial malformations, cleft palate, limb malrotation, anal atresia, internal hydrocephaly, anophthalmia and fused bones. The dose of 150 mg/kg/day in rabbits resulted in external fetal malformations (partially opened eyes) and minor blood vessel and skeletal variations.

In rats, malformations including micrognathia and persistent ductus arteriosus could be observed in the absence of maternal toxicity at doses equal to or greater than 30 and 80 mg/kg/day, approximately 5% and 13% of the MHRD, respectively.

8.2 Lactation

Risk Summary

There is no information regarding the presence of deferiprone in human milk, the effects on the breastfed child, or the effects on milk production.

Because of the potential for serious adverse reactions in the breastfed child, including the potential for tumorigenicity shown for deferiprone in animal studies, advise patients that breastfeeding is not recommended during treatment with FERRIPROX, and for at least 2 weeks after the last dose.

8.3 Females and Males of Reproductive Potential

Pregnancy Testing

Pregnancy testing is recommended for females of reproductive potential prior to initiating FERRIPROX.

Contraception

Females

FERRIPROX can cause embryo-fetal harm when administered to a pregnant woman [see Use in Specific Populations (8.1)]. Advise female patients of reproductive potential to use effective contraception during treatment with FERRIPROX and for at least 6 months after the last dose.

Males

Based on genotoxicity findings, advise males with female partners of reproductive potential to use effective contraception during treatment with FERRIPROX and for at least 3 months after the last dose [see Nonclinical Toxicology (13.1)].

8.4 Pediatric Use

The safety and effectiveness of FERRIPROX for the treatment of transfusional iron overload due to thalassemia syndromes have been established in pediatric patients 3 years of age and older. Use of FERRIPROX for this indication is supported by evidence of efficacy from clinical trials in adult patients with thalassemia and evidence of safety in pediatric patients with sickle cell disease.

The safety and effectiveness of FERRIPROX for the treatment of transfusional iron overload due to sickle cell disease or other anemias have been established in 86 pediatric patients 3 to 16 years of age, among the 152 patients treated with FERRIPROX Tablets or Oral Solution in an adequate and well-controlled study [see Adverse Reactions (6.1) and Clinical Studies (14.2)]. The study included 56 patients 3 to <12 years of age and 30 patients 12 to 16 years of age. Seventy-six percent of these patients had sickle cell disease. The recommended starting dose and dose-modifications are the same for children and adults [see Indications and Usage (1), Dosage and Administration (2.1), and Clinical Studies (14)].

Fourteen patients with spherocytosis (including hereditary) (ages 3-15), two patients with pyruvate kinase deficiency (ages 4 and 6), two patients with dyserythropoietic anemia (ages 10-12) and two patients with hemolytic anemia (ages 8 and 10 years old) were treated with FERRIPROX in the clinical trial, LA38-0411.

A US registry established from December 2011 through December 2019, contains 125 patients from 4 to < 17 years old who have received FERRIPROX and have sickle cell disease. The adverse reactions, including agranulocytosis, seen in the 8 year period of the registry are similar to those seen in the most recent clinical studies.

Safety and effectiveness of FERRIPROX Oral Solution has not been established in pediatric patients with chronic iron overload due to blood transfusions who are less than 3 years of age.

8.5 Geriatric Use

Clinical studies of deferiprone did not include sufficient numbers of subjects aged 65 and over to determine whether they respond differently from younger subjects. Other reported clinical experience has not identified differences in responses between the elderly and younger patients.

10 OVERDOSAGE

No cases of acute overdose have been reported. There is no specific antidote to FERRIPROX overdose.

Neurological disorders such as cerebellar symptoms, diplopia, lateral nystagmus, psychomotor slowdown, hand movements and axial hypotonia have been observed in children treated with 2.5 to 3 times the recommended dose for more than one year. The neurological disorders progressively regressed after deferiprone discontinuation.

11 DESCRIPTION

FERRIPROX Oral Solution (deferiprone) contains 100 mg/mL deferiprone (3-hydroxy-1,2-dimethylpyridin-4-one), a synthetic, orally active, iron-chelating agent. The molecular formula for deferiprone is C7H9NO2 and its molecular weight is 139.15 g/mol. Deferiprone has the following structural formula:

Deferiprone is a white to pinkish-white powder. It is sparingly soluble in deionized water (14.3 mg/mL) and has a melting point range of 272 °C - 278 °C.

FERRIPROX Oral Solution is a clear, reddish orange colored solution. Each mL of oral solution contains 100 mg deferiprone and the following inactive ingredients: purified water, hydroxyethylcellulose, glycerin, hydrochloric acid, artificial cherry flavor, peppermint oil, FD&C Yellow No. 6, and sucralose.

12 CLINICAL PHARMACOLOGY

12.1 Mechanism of Action

Deferiprone is a chelating agent with an affinity for ferric ions (iron III). Deferiprone binds with ferric ions to form neutral 3:1 (deferiprone:iron) complexes that are stable at physiological pH.

12.2 Pharmacodynamics

No clinical studies were performed to assess the relationship between the dose of deferiprone and the amount of iron eliminated from the body.

Cardiac Electrophysiology

At the maximum approved recommended dose, deferiprone does not prolong the QT interval to any clinically relevant extent.

12.3 Pharmacokinetics

The mean Cmax and AUC of deferiprone was 20 mcg/mL and 50 mcg∙h/mL, respectively, in healthy subjects. The dose proportionality of deferiprone over the approved recommended dosage range is unknown.

Absorption

Deferiprone appeared in the blood within 5 to 10 minutes after oral administration. Peak serum concentration of deferiprone was reached approximately 1 to 2 hours after a single dose.

Effect of Food

No clinically significant differences in the pharmacokinetics of deferiprone were observed following administration with food.

Elimination

The elimination half-life of deferiprone is approximately 2 hours.

Metabolism

Deferiprone is metabolized primarily by UGT1A6. The major metabolite of deferiprone is the 3-O-glucuronide, which lacks iron binding capability.

Excretion

Following oral administration, 75% to 90% of the administered dose was recovered in urine (primarily as metabolite) in the first 24 hours.

Specific Populations

No clinically significant differences in the pharmacokinetics of deferiprone were observed based on sex, race/ethnicity, body weight, mild to severe (eGFR 15 to 89 mL/min/1.73 m^2) renal impairment, or mild (Child Pugh Class A) to moderate (Child Pugh Class B) hepatic impairment. The effect of age, including geriatric or pediatric populations, end stage renal disease or severe (Child Pugh Class C) hepatic impairment on the pharmacokinetics of deferiprone is unknown.

Drug Interaction Studies

In Vitro Studies

UGTIA6 Inhibitors: Phenylbutazone (UGT1A6 inhibitor) decreased glucuronidation of deferiprone by up to 78%.

Polyvalent Cations: Deferiprone has the potential to bind polyvalent cations (e.g., iron, aluminum, and zinc).

13 NONCLINICAL TOXICOLOGY

13.1 Carcinogenesis, Mutagenesis, Impairment of Fertility

Carcinogenicity studies have not been conducted with deferiprone. However, in view of the genotoxicity results, and the findings of mammary gland hyperplasia and mammary gland tumors in rats treated with deferiprone in the 52-week toxicology study, tumor formation in carcinogenicity studies must be regarded as likely.

Deferiprone was positive in a mouse lymphoma cell assay in vitro. Deferiprone was clastogenic in an in vitro chromosomal aberration test in mice and in a chromosomal aberration test in Chinese Hamster Ovary cells. Deferiprone given orally or intraperitoneally was clastogenic in a bone marrow micronucleus assay in non-iron-loaded mice. A micronucleus test was also positive when mice predosed with iron dextran were treated with deferiprone. Deferiprone was not mutagenic in the Ames bacterial reverse mutation test.

A fertility and early embryonic development study of deferiprone was conducted in rats. Sperm counts, motility and morphology were unaffected by treatment with deferiprone. There were no effects observed on male or female fertility or reproductive function at the highest dose which was 25% of the MRHD.

14 CLINICAL STUDIES

14.1 Transfusional Iron Overload in Patients with Thalassemia Syndromes

In a prospective, planned, pooled analysis of patients with thalassemia syndromes from several studies, the efficacy of deferiprone was assessed in transfusion-dependent iron overload patients in whom previous iron chelation therapy had failed or was considered inadequate due to poor tolerance. The main criterion for chelation failure was serum ferritin > 2,500 mcg/L before treatment with deferiprone. Deferiprone therapy (35-99 mg/kg/day) was considered successful in individual patients who experienced a ≥ 20% decline in serum ferritin within one year of starting therapy.

Data from a total of 236 patients were analyzed. Of the 224 patients with thalassemia who received deferiprone monotherapy and were eligible for serum ferritin analysis, 105 (47%) were male and 119 (53%) were female. The mean age of these patients was 18.2 years (range 2 to 62; 91 patients were <17).

For the patients in the analysis, the endpoint of at least a 20% reduction in serum ferritin was met in 50% (of 236 subjects), with a 95% confidence interval of 43% to 57%.

A small number of patients with thalassemia and iron overload were assessed by measuring the change in the number of milliseconds (ms) in the cardiac MRI T2* value before and after treatment with deferiprone for one year. There was an increase in cardiac MRI T2* from a mean at baseline of 11.8 ± 4.9 ms to a mean of 15.1 ± 7.0 ms after approximately one year of treatment. The clinical significance of this observation is not known.

14.2 Transfusional Iron Overload in Patients with Sickle Cell Disease and other Anemias

Study LA38-0411, an actively-controlled non-inferiority study compared the efficacy of FERRIPROX to that of deferoxamine in patients with sickle cell disease and other transfusion-dependent anemias by evaluating liver iron concentration (LIC). The efficacy of FERRIPROX was established based upon the change in LIC from baseline after 12 months of FERRIPROX (75 or 99 mg/kg/day) compared to deferoxamine (20 or 40 mg/kg (pediatric patients); 40 or 50 mg/kg (adult patients)). Patient enrollment was stopped following an interim analysis. After adjusting for the type I (alpha) error, the non-inferiority criterion was established as the upper limit of the 96.01% confidence interval for the difference between treatments being ≤2 mg/g dry weight (dw).

Data from 185 patients (122 on FERRIPROX and 63 on deferoxamine) were available. Among the 122 FERRIPROX treated patients, the mean age was 15.9 years (range 3-46); 57.4% were male; 75.4% were White, 17.2% were Black and 7.4% were Multi-racial; 85% were diagnosed with Sickle Cell Disease and 15% with other anemias. Over 12 months, the Least Squares estimate of mean decrease from baseline in LIC was 4.13 ± 0.50 mg/g dw for FERRIPROX and 4.38 ± 0.59 mg/g dw for deferoxamine, and the non-inferiority criterion was met.

Upon completion of the first year of therapy in the non inferiority study, 89 patients from the FERRIPROX group opted to continue with treatment and 45 from the deferoxamine group opted to switch to FERRIPROX treatment. This group continued for up to an additional 2 years. LIC continued to decrease over time, with the mean value dropping from 14.93 mg/g dw at baseline to 12.30 mg/g dw after one year of treatment, to 11.19 mg/g dw after two years of treatment, and to 10.45 mg/g dw after three years of treatment.

16 HOW SUPPLIED/STORAGE AND HANDLING

FERRIPROX® Oral Solution (deferiprone) is provided in amber polyethylene terephthalate (PET) bottles with child resistant closures (polypropylene). Each pack contains one bottle of 500 mL oral solution and a graduated measuring cup (polypropylene).

Oral solution, 100 mg/mL (50 g/500 mL), NDC 10122-101-50

Store at 20°C to 25°C (68°F to 77°F); excursions permitted to 15°C to 30°C (59°F to 86°F) [see USP Controlled Room Temperature].

Store in the original bottle and carton to protect from light.

After first opening of the bottle, discard any unused portion after 35 days.

17 PATIENT COUNSELING INFORMATION

Advise the patient to read the FDA-approved patient labeling (Medication Guide and Instructions for Use)

- Instruct patients and their caregivers to store FERRIPROX Oral Solution at 68°F to 77°F (20°C to 25°C); excursions permitted to 59°F to 86°F (15°C to 30°C) [see USP Controlled Room Temperature]. Store in the originally supplied bottle and carton to protect from light.
- Advise patients to use the measuring cup provided with FERRIPROX Oral Solution to measure the volume prescribed. Instruct patients to add about 10-15 mL of water to the measuring cup and swirl it around to mix the water with any remaining medicine in the cup and drink the mixture. The measuring cup should be hand-washed with water after use.
- Advise patients to take the first dose of FERRIPROX Oral Solution in the morning, the second dose at midday, and the third dose in the evening. Clinical experience suggests that taking FERRIPROX Oral Solution with meals may reduce nausea.If a dose of this medicine has been missed, take it as soon as possible. However, if it is almost time for the next dose, skip the missed dose and go back to the regular dosing schedule. Do not catch-up or double doses.
- Inform patients of the risks of developing agranulocytosis and the need for regular blood testing before and during their treatment to monitor for decreases in their ANC. Instruct them to immediately interrupt therapy and report to their physician if they experience any symptoms of infection such as fever, sore throat or flu-like symptoms [see Dosage and Administration (2.1) and Warnings and Precautions (5.1)] in order to check their ANC within 24 hours. Advise them if they are unable to reach their physician, seek care from another provider so as not to delay medical care.
- Inform patients of the risk of abnormal liver transaminases and the need for regular blood testing before and during their treatment to monitor for increases in ALT [see Dosage and Administration (2.1) and Warnings and Precautions (5.2)].
- Inform patients of the risk of zinc deficiency and the need for regular blood testing before and during their treatment to monitor for reductions in zinc [see Dosage and Administration (2.1) and Warnings and Precautions (5.3)].
- Advise patients to contact their physician in the event of overdose.
- Inform patients that their urine might show a reddish/brown discoloration due to the excretion of the iron-deferiprone complex. This is a very common sign of the desired effect, and it is not harmful.

Embryo-Fetal toxicity

Advise pregnant women and females of reproductive potential of the potential risk to a fetus. Advise females to inform their healthcare provider of a known or suspected pregnancy [see Warnings and Precautions (5.4) and Use in Specific Populations (8.1)]. Advise female patients of reproductive potential to use effective contraception during treatment with FERRIPROX and for at least six months after the last dose [see Use in Specific Populations (8.1, 8.3)]. Advise males with female partners of reproductive potential to use effective contraception during treatment with FERRIPROX and for at least three months after the last dose [see Use in Specific Populations (8.3) and Nonclinical Toxicology (13.1)].

Lactation

Advise females not to breastfeed during treatment with FERRIPROX and for at least 2 weeks after the last dose [see Use in Specific Populations (8.2)].

Distributed by Chiesi USA, Inc., Cary, NC 27518. Manufactured by Apotex Inc., Toronto, Ontario, Canada, M9L 1T9.

US-643-s4-SPL

Medication Guide
FERRIPROX (Feh ri prox) Oral Solution
(deferiprone)
oral solution, for oral use
100 mg/mL

What is the most important information I should know about FERRIPROX Oral Solution?
FERRIPROX Oral Solution can cause serious side effects, including a very low white blood cell count. One type of white blood cell that is important for fighting infections is called a neutrophil. If your neutrophil count is low (neutropenia), you may be at risk of developing a serious infection that can lead to death. Neutropenia is common with FERRIPROX Oral Solution and can become severe in some people. Severe neutropenia is known as agranulocytosis. If you develop agranulocytosis, you will be at risk of developing serious infections that can lead to death.
Your healthcare provider will do a blood test before you start FERRIPROX Oral Solution and regularly during treatment to check your neutrophil count. If you develop neutropenia, your healthcare provider should check your blood counts every day until your white blood cell count improves. Your healthcare provider may temporarily stop treatment with FERRIPROX Oral Solution if you develop neutropenia or infection.
Stop taking FERRIPROX Oral Solution and call your healthcare provider or get medical help right away if you develop any of these symptoms of infection:

- fever
- sore throat or mouth sores
- flu-like symptoms
- chills and severe shaking

It is important for you to have your white blood cell count checked within 24 hours of developing symptoms of an infection to see if you have severe neutropenia (agranulocytosis). Do not delay getting medical care if you are unable to reach your healthcare provider.
See “What are the possible side effects of FERRIPROX Oral Solution?” for more information about side effects.

What is FERRIPROX Oral Solution?
FERRIPROX Oral Solution is a prescription medicine used to treat iron overload from blood transfusions in adults and children 3 years of age and older with:

- thalassemia syndromes.
- sickle cell disease or other anemias.

It is not known if FERRIPROX Oral Solution is safe and effective to treat iron overload due to blood transfusions:

- in people with myelodysplastic syndrome or Diamond Blackfan anemia
- in children less than 3 years of age

Do not take FERRIPROX Oral Solution if you are allergic to deferiprone or any of the ingredients in FERRIPROX Oral Solution. See the end of this Medication Guide for a complete list of ingredients in FERRIPROX Oral Solution.

Before taking FERRIPROX Oral Solution, tell your healthcare provider about all of your medical conditions, including if you:

- have liver problems
- are pregnant or plan to become pregnant. FERRIPROX Oral Solution can harm your unborn baby. You should avoid becoming pregnant during treatment with FERRIPROX Oral Solution. Tell your healthcare provider right away if you become pregnant or think you may be pregnant during treatment with FERRIPROX Oral Solution.
  Females who are able to become pregnant:
  - Your healthcare provider should do a pregnancy test before you start treatment with FERRIPROX Oral Solution.
  - You should use effective birth control during treatment with FERRIPROX Oral Solution and for at least 6 months after the last dose.
  Males with female partners who are able to become pregnant:
  - You should use effective birth control during treatment with FERRIPROX Oral Solution and for at least 3 months after the last dose.
- are breastfeeding or plan to breastfeed. It is not known if FERRIPROX Oral Solution passes into your breast milk. Do not breastfeed during treatment with FERRIPROX Oral Solution and for at least 2 weeks after the last dose.

Tell your healthcare provider about all the medicines you take, including prescription and over-the-counter medicines, vitamins and herbal supplements.

How should I take FERRIPROX Oral Solution?
Read the Instructions for Use for detailed instructions about how to measure and take a dose of FERRIPROX Oral Solution.

- Take FERRIPROX Oral Solution exactly as your healthcare provider tells you.
- Your healthcare provider will prescribe FERRIPROX Oral Solution based on your body weight.
- Your healthcare provider will check your body iron level during treatment with FERRIPROX Oral Solution and may change your dose if needed. Your healthcare provider may also change your dose of FERRIPROX Oral Solution if you have certain side effects. Do not change your dose of FERRIPROX Oral Solution unless your healthcare provider tells you to.
- Use the measuring cup that comes with FERRIPROX Oral Solution to measure your prescribed dose.
- Take FERRIPROX Oral Solution 3 times each day. Take your first dose in the morning, the second dose at mid-day, and the third dose in the evening.
- Taking FERRIPROX Oral Solution with meals may help reduce nausea.
- If you must take a medicine to treat indigestion (antacid), or supplements that contain iron, aluminum, or zinc during treatment with FERRIPROX Oral Solution, allow at least 4 hours between taking FERRIPROX Oral Solution and these products.
- If you take too much FERRIPROX Oral Solution, call your healthcare provider.
- If you miss a dose, take it as soon as you remember. If it is almost time for your next dose, skip the missed dose and then continue with your regular schedule. Do not try to catch-up or take 2 doses at the same time to make up for a missed dose.

What are the possible side effects of FERRIPROX Oral Solution?
FERRIPROX Oral Solution can cause serious side effects, including:

- See “What is the most important information I should know about FERRIPROX Oral Solution?”
- Increased liver enzyme levels in your blood. Your healthcare provider should do blood tests to check your liver function before you start and then monthly during treatment with FERRIPROX Oral Solution. Your healthcare provider may temporarily stop treatment with FERRIPROX Oral Solution if you develop increased liver enzyme levels and they continue to be increased.
- Decreased levels of zinc in your blood. Your healthcare provider will do blood tests to check your zinc levels before you start and during treatment with FERRIPROX Oral Solution, and may prescribe a zinc supplement for you if your zinc levels are low.

The most common side effects of FERRIPROX Oral Solution in people with thalassemia include:

- nausea
- joint pain

- vomiting
- abnormal liver function tests

- stomach-area (abdominal) pain
- low white blood cells

The most common side effects of FERRIPROX Oral Solution in people with sickle cell disease or other anemias include:

- fever
- headache
- sickle cell anemia with crisis
- joint pain
- low white blood cells

- stomach-area (abdominal) pain
- vomiting
- back pain
- mouth and throat pain
- cough

- bone pain
- pain in arms or legs
- abnormal liver function tests
- common cold
- nausea

FERRIPROX Oral Solution may cause a change in urine color to reddish-brown. This is not harmful and is expected during treatment with FERRIPROX Oral Solution.
These are not all of the possible side effects of FERRIPROX Oral Solution.
Call your doctor for medical advice about side effects. You may report side effects to FDA at 1-800-FDA-1088.

How should I store FERRIPROX Oral Solution?

- Store FERRIPROX Oral Solution at room temperature between 68°F to 77°F (20°C to 25°C).
- Store FERRIPROX Oral Solution in the original bottle and carton to protect from light.
- After first opening, use a bottle of FERRIPROX Oral Solution within 35 days. After 35 days, discard the bottle and any unused FERRIPROX Oral Solution.

Keep FERRIPROX Oral Solution and all medicines out of the reach of children.

General information about the safe and effective use of FERRIPROX Oral Solution.
Medicines are sometimes prescribed for purposes other than those listed in a Medication Guide. Do not use FERRIPROX Oral Solution for a condition for which it was not prescribed. Do not give FERRIPROX Oral Solution to other people, even if they have the same symptoms that you have. It may harm them. You can ask your pharmacist or healthcare provider for information about FERRIPROX Oral Solution that is written for health professionals.

What are the ingredients in FERRIPROX Oral Solution?
Active ingredient: deferiprone
Inactive ingredients: purified water, hydroxyethylcellulose, glycerin, hydrochloric acid, artificial cherry flavor, peppermint oil, FD&C Yellow No. 6, and sucralose.
Distributed by: Chiesi USA, Inc., Cary, NC 27518.
Manufactured by: Apotex Inc., Toronto, Ontario, Canada, M9L 1T9.
CTFD-016-0521-02-SPL
For more information, call 1-888-661-9260.

This Medication Guide has been approved by the U.S. Food and Drug Administration.

Revised: 11/2021

Instructions for Use

FERRIPROX (Feh' ri prox) Oral Solution

(deferiprone)

oral solution, for oral use

100 mg/mL

Read this Instructions for Use before taking FERRIPROX Oral Solution or giving FERRIPROX Oral Solution to your child and each time you get a refill. There may be new information. This information does not take the place of talking to your healthcare provider about your or your child's medical condition or treatment.

Important information:

- Store FERRIPROX Oral Solution at room temperature between 68°F to 77°F (20°C to 25°C).
- Store FERRIPROX Oral Solution in the original bottle and carton to protect from light.
- After first opening, use a bottle of FERRIPROX Oral Solution within 35 days. After 35 days, discard the bottle and any unused FERRIPROX Oral Solution.

Keep FERRIPROX Oral Solution and all medicines out of the reach of children.

Supplies needed to measure and take a dose of FERRIPROX Oral Solution (See Figure A):

- 1 bottle of FERRIPROX Oral Solution
- 1 measuring cup (supplied with each bottle of FERRIPROX Oral Solution). The measuring cup has markings for teaspoons (TSP) and milliliters (mL). Note: 1 TSP is equal to 5 mL.

Figure A

If you do not receive a measuring cup with your FERRIPROX Oral Solution, ask your pharmacist. Only use the measuring cup that comes with FERRIPROX Oral Solution to make sure that you measure the right amount of medicine.

Step 1: To open the bottle of FERRIPROX Oral Solution, remove the outer plastic wrapper from the child-resistant cap. Push down on the child-resistant cap and turn the cap in the direction of the arrow (See Figure B).

Figure B

Step 2: Pour the prescribed dose of FERRIPROX Oral Solution into the measuring cup (See Figure C).

Figure C

Step 3: Put the child-resistant cap back on the FERRIPROX Oral Solution bottle and turn it in the direction of the arrow. (See Figure D)

Figure D

Step 4: Swallow the prescribed dose of FERRIPROX Oral Solution (See Figure E).

Figure E

Step 5: Add about 10 to 15 mL of water to the measuring cup (See Figure F). Gently swirl the measuring cup to mix the water and any FERRIPROX Oral Solution left in the measuring cup (See Figure G). Drink all the mixture in the measuring cup (See Figure H).

Figure F

Figure G

Figure H

Step 6: Hand-wash the measuring cup with water.

Step 7: Keep the measuring cup with the bottle of FERRIPROX Oral Solution.

This Instructions for Use has been approved by the U.S. Food and Drug Administration.

Distributed by:
Chiesi USA, Inc., Cary, NC 27518.

Manufactured by:
Apotex Inc., Toronto, Ontario, Canada, M9L 1T9.

Revised: 04/2021.
CTFD-021-0620-01-SPL-1

PACKAGE LABEL.PRINCIPAL DISPLAY PANEL SECTION

Chiesi USA, Inc., NDC 10122-101-50

FERRIPROX oral solution

100 mg/mL (50 g/500 mL)

Rx only

500 mL